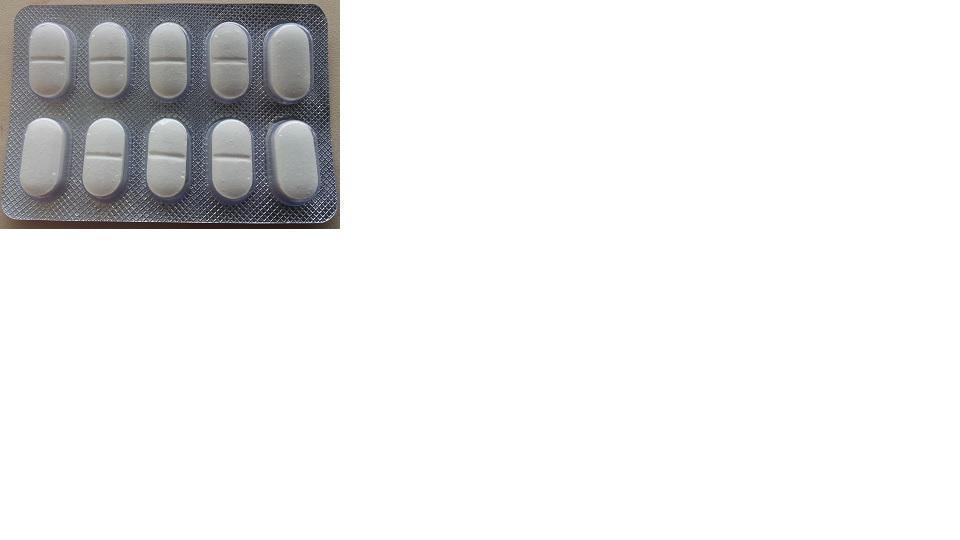 DRUG LABEL: ACETAMINOPHEN SINUS CONGESTION AND PAIN
NDC: 46084-101 | Form: TABLET
Manufacturer: A P J Laboratories Limited
Category: otc | Type: HUMAN OTC DRUG LABEL
Date: 20130606

ACTIVE INGREDIENTS: ACETAMINOPHEN 325 mg/1 1; PHENYLEPHRINE HYDROCHLORIDE 5 mg/1 1
INACTIVE INGREDIENTS: CALCIUM PHOSPHATE, DIBASIC, ANHYDROUS 160 mg/1 1; CELLULOSE, MICROCRYSTALLINE 120 mg/1 1; STARCH, CORN 30 mg/1 1; BUTYLATED HYDROXYTOLUENE .5 mg/1 1; METHYLPARABEN .8 mg/1 1; PROPYLPARABEN .4 mg/1 1; SODIUM STARCH GLYCOLATE TYPE A POTATO 20 mg/1 1; TALC 15 mg/1 1; MAGNESIUM STEARATE 13 mg/1 1; SALICYLIC ACID 4 mg/1 1; CROSCARMELLOSE SODIUM 7 mg/1 1; SODIUM LAURYL SULFATE 2 mg/1 1; ISOPROPYL ALCOHOL 130 mg/1 1; METHYLENE CHLORIDE 280 mg/1 1; TITANIUM DIOXIDE 1.5 mg/1 1; HYPROMELLOSES 3 mg/1 1

ACTIVE INGREDIENT

ACETAMINOPHEN 325 mg

PHENYLEPHRINE HYDROCHLORIDE 5mg

PURPOSE

•Alleviates Sinus Headache & Pain (Acetaminophen)

•Relieves Sinus Pressure Clears Nasal Congestion (Phenylephrine HCl)

Keep out of reach of children.

INDICATIONS AND USAGE

for the temporary relief of:

• headache

•sinus

•congestion and pressurenasal congestion

•minor aches and pains

•helps decongest sinus openings and passages

•promotes sinus drainage

•helps clear nasal passages

WARNINGS

Liver warning:

This product contains acetaminophen. Severe liver damage may occur if you take

■ more than 12 gelcaps in 24 hours, which is the maximum daily amount

■ with other drugs containing acetaminophen

■ 3 or more alcoholic drinks every day while using this product

Overdose warning:

■ Taking more than the recommended dose (overdose) may cause liver damage.

■ In case of overdose, get medical help or contact a Poison Control Center right away. (1-800-222-1222) Quick medical attention is critical for adults as well as for children even if you do not notice any signs or symptoms.

Directions

■ Do not take more than directed (see overdose warning)

■ Adults and children 12 years and over: Take 2 gelcaps every 4 hoursdo not take more than 12 gelcaps in 24 hours

■ Children under 12 years: Do not use this adult product in children under 12 years of age

INACTIVE INGREDIENT

•CALCIUM PHOSPHATE, DIBASIC, ANHYDROUS

•CELLULOSE, MICROCRYSTALLINE

•STARCH, CORN

•BUTYLATED HYDROXYTOLUENE

•METHYLPARABEN

•PROPYLPARABEN

•SODIUM STARCH GLYCOLATE TYPE A POTATO

•TALC

•MAGNESIUM STEARATE

•SALICYLIC ACID

•CROSCARMELLOSE SODIUM

•SODIUM LAURYL SULFATE

•ISOPROPYL ALCOHOL

•METHYLENE CHLORIDE

•TITANIUM DIOXIDE

•HYPROMELLOSES